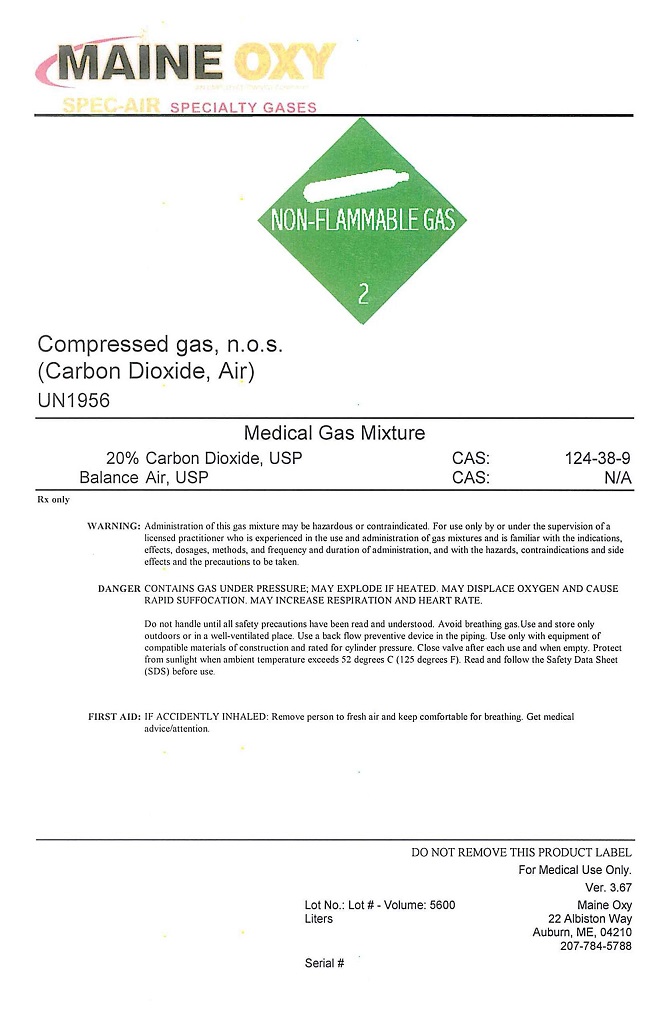 DRUG LABEL: Carbon Dioxide Air
NDC: 51887-401 | Form: GAS
Manufacturer: Maine Oxy-Acetylene Supply Company
Category: animal | Type: PRESCRIPTION ANIMAL DRUG LABEL
Date: 20251120

ACTIVE INGREDIENTS: Carbon Dioxide 200 mL/1 L; AIR 800 mL/1 L

Carbon Dioxide Air mix

PACKAGE LABEL

MAINE OXY SPEC-AIR SPECIALTY GASES
NON-FLAMMABLE GAS 2 Compressed Gas, n.o.s. (Carbon Dioxide, Air) UN1956
Medical Gas Mixture 20% Carbon Dioxide, USP CAS: 124-38-9 Balance Air, USP CAS: N/A Rx only
WARNING: Administration of this gas mixture may be hazardous or contraindicated. For use only by or under the supervision of a licensed practitioner who is experienced in the use and administration of gas mixtures and is familiar with the indications, effects, dosages, methods, and frequency and duration of administration, and with the hazards, contraindications, and side effects and the precautions to be taken.
DANGER: CONTAINS GAS UNDER PRESSURE; MAY EXPLODE IF HEATED. MAY DISPLACE OXYGEN AND CAUSE RAPID SUFFOCATION. MAY INCREASE RESPIRATION AND HEART RATE.
Do not handle until all safety precautions have been read and understood. Keep and store away from clothing and other combustible materials. Keep valves and fittings free from grease and oil. Use and store only outdoors or in a well-ventilated place. In case of fire: Stop leak if safe to do so. Use a back flow preventive device in the piping. Use only with equipment of compatible materials of construction and rated for cylinder pressure. Use only with equipment cleaned for oxygen service. Open valve slowly. Close valve after each use and when empty. Protect from sunlight when Protect from sunlight when ambient temperature exceeds 52 degrees C (125 degrees F). Read and follow the Safety Data Sheet (SDS) before use.
FIRST AID: IF ACCIDENTLY INHALED: Remove person to fresh air and keep comfortable for breathing. Get medical advice/attention.
DO NOT REMOVE THIS PRODUCT LABEL
For Medical Use Only. Ver. 3.67 Lot No.: Lot# - Volume: 5600 Serial #
MAINE OXY 22 ALBISTON WAY . AUBURN, ME 04210 . 207-784-57